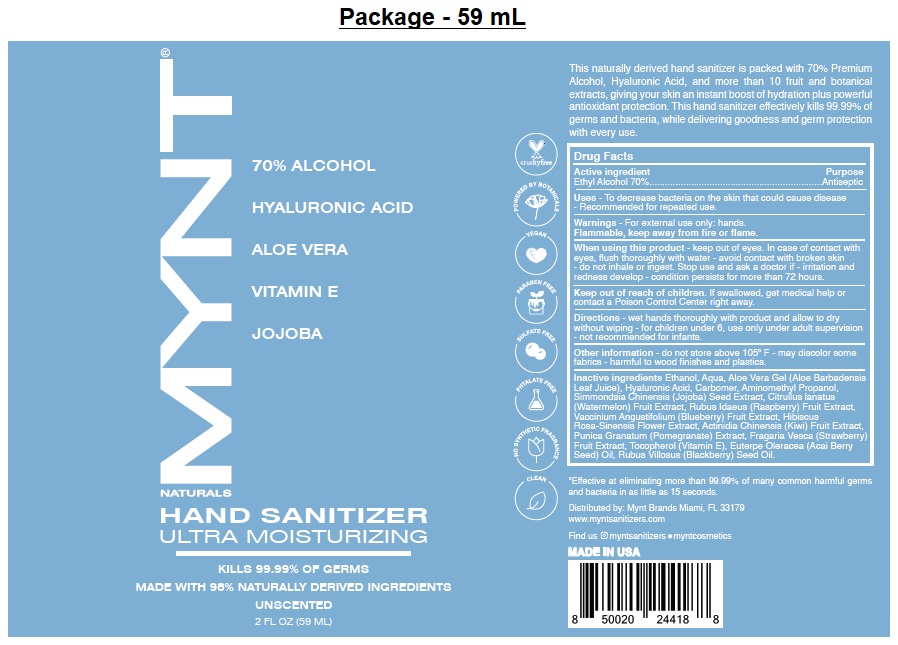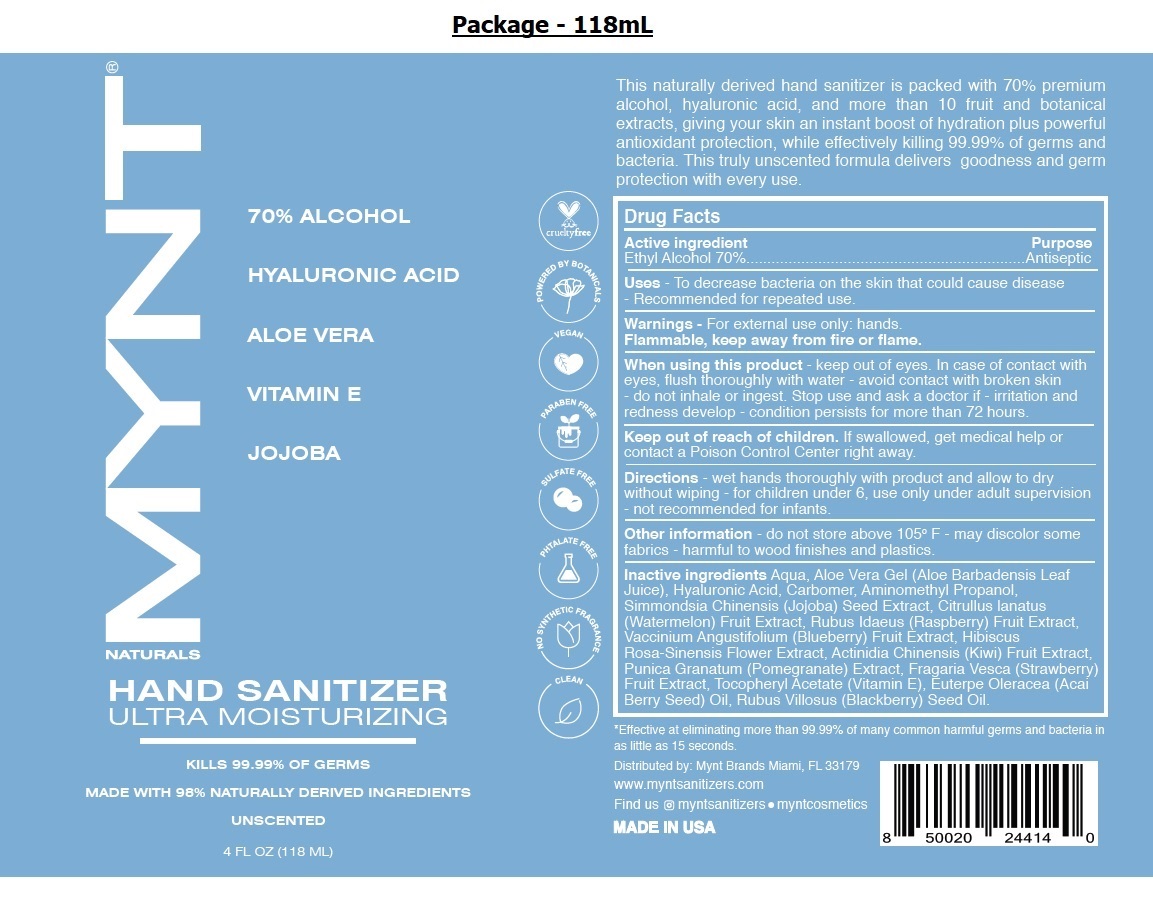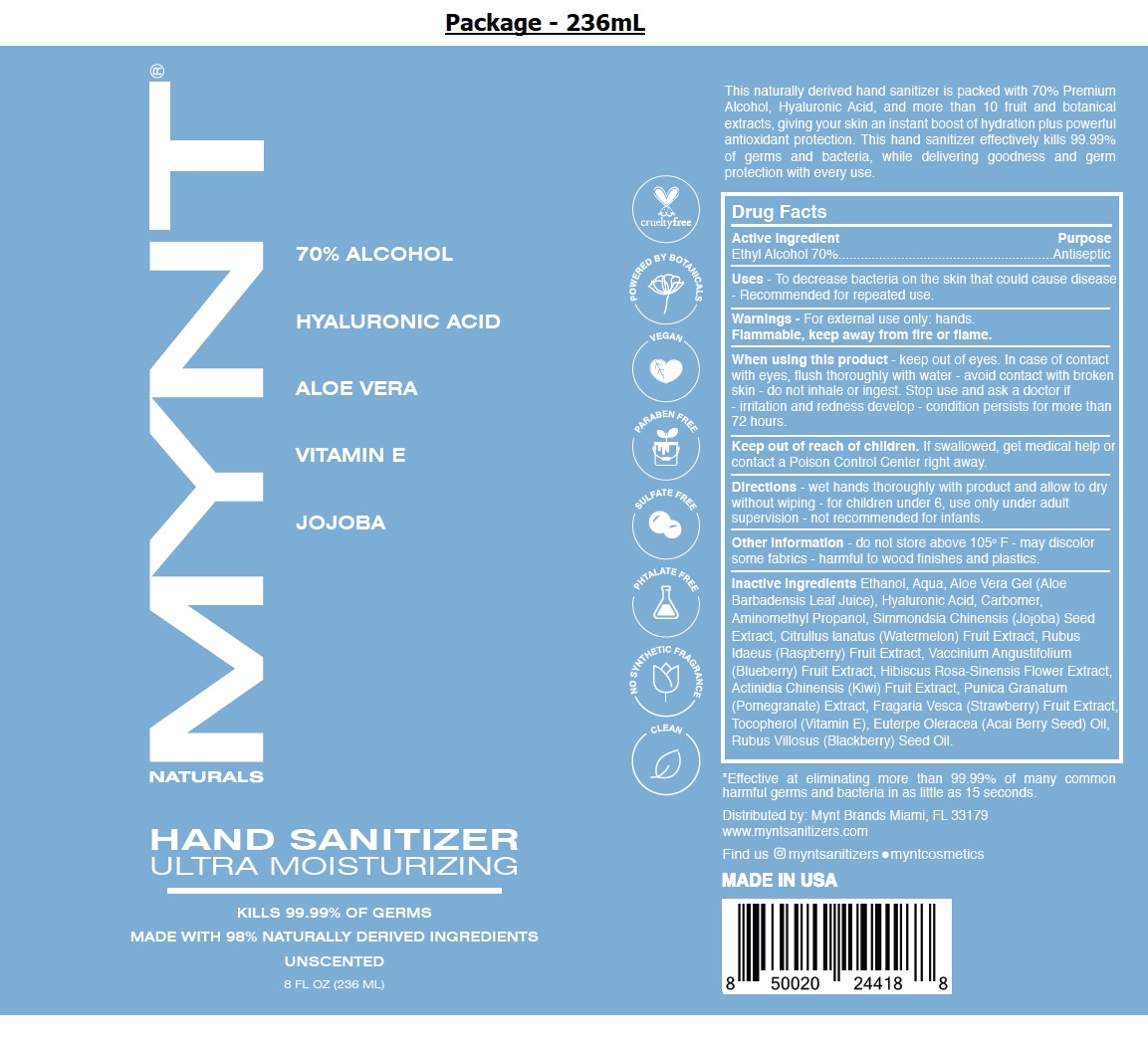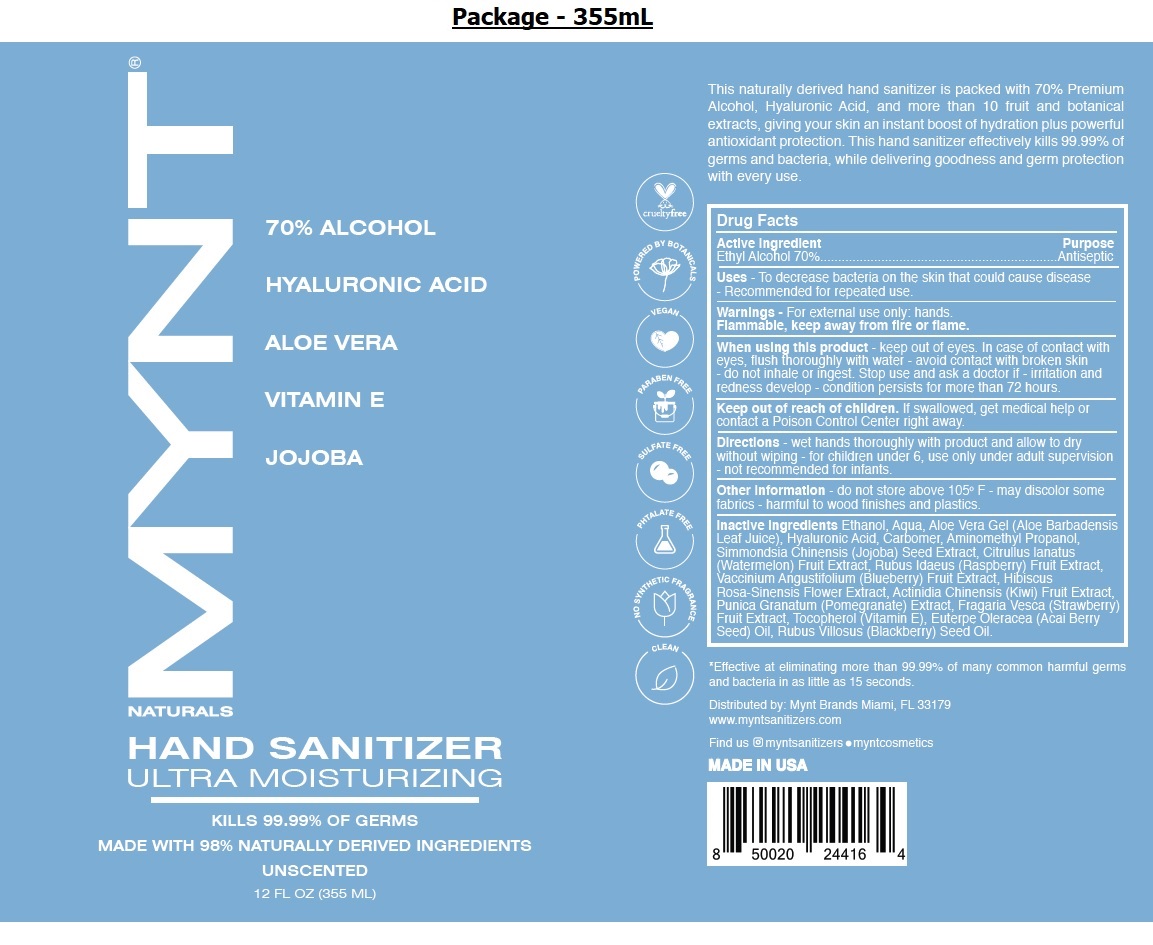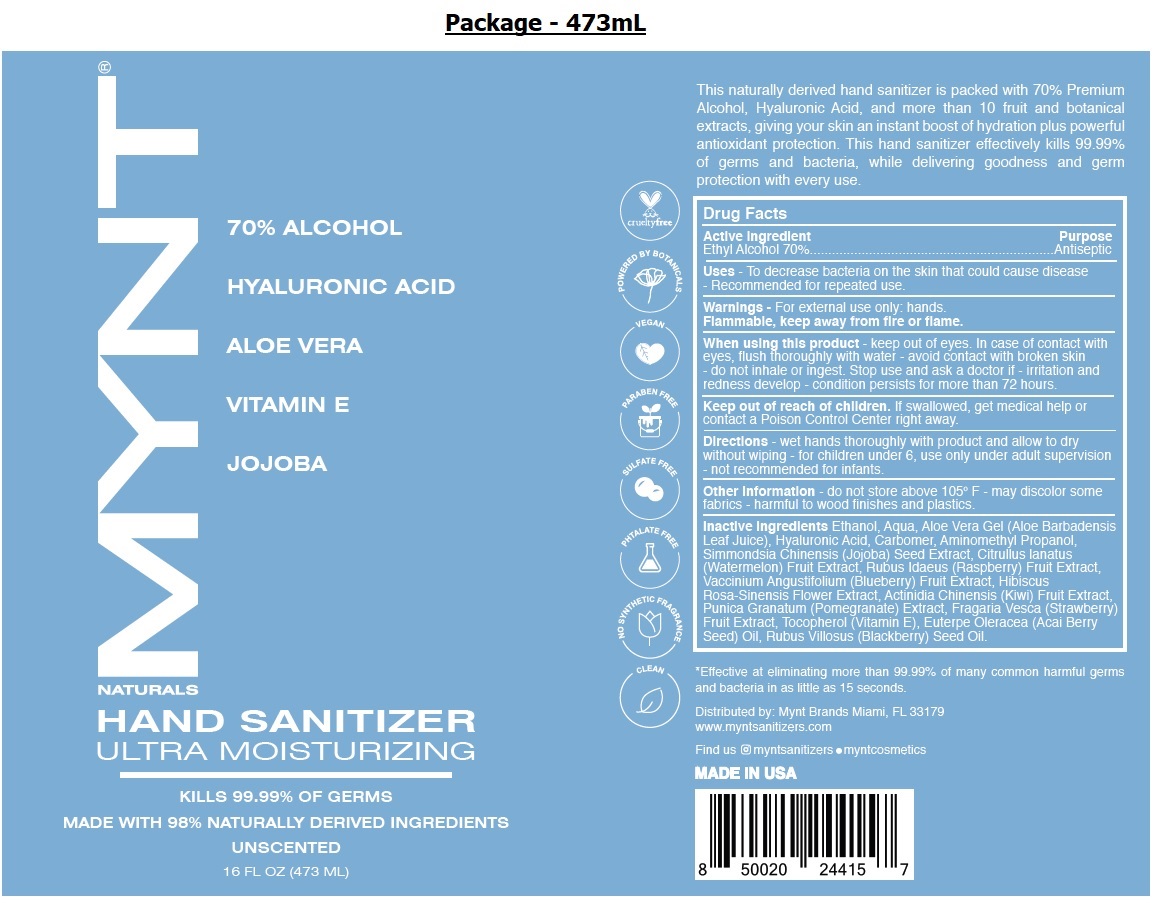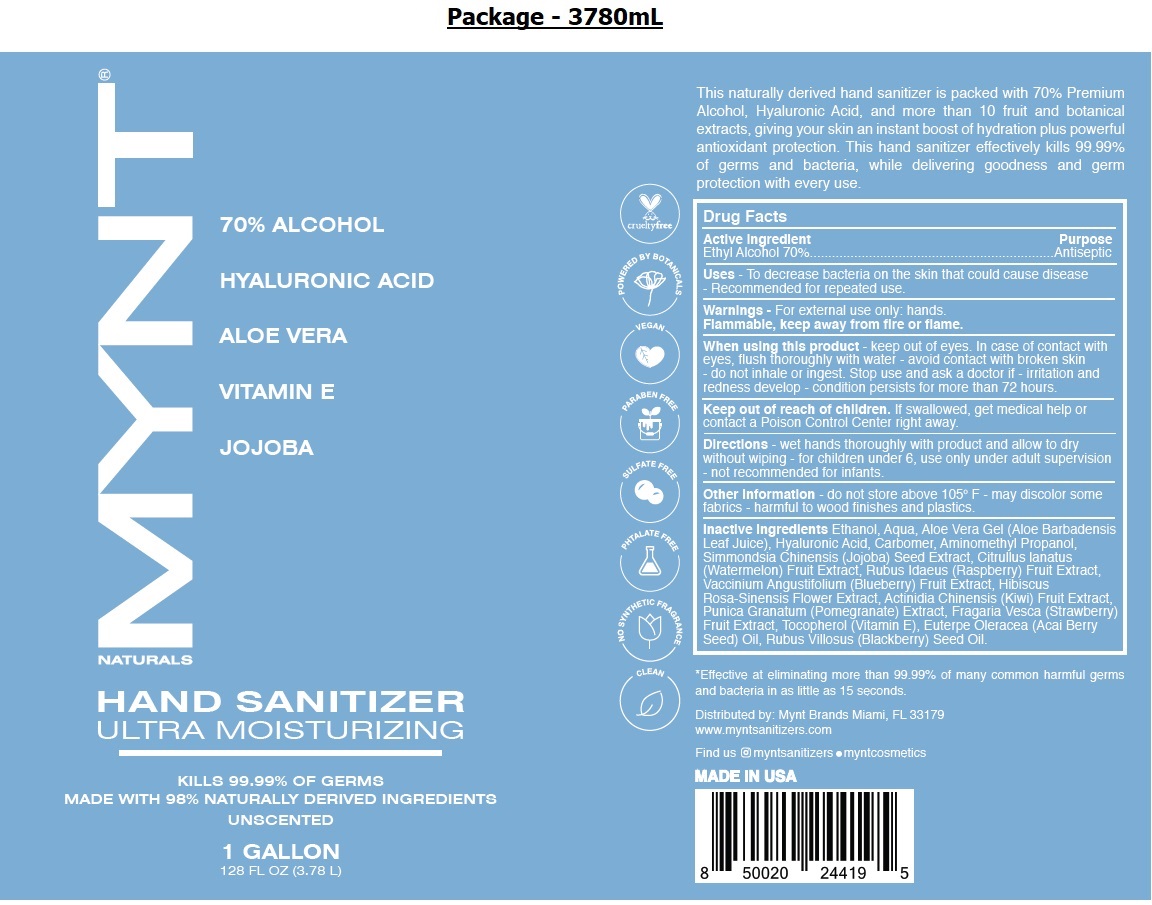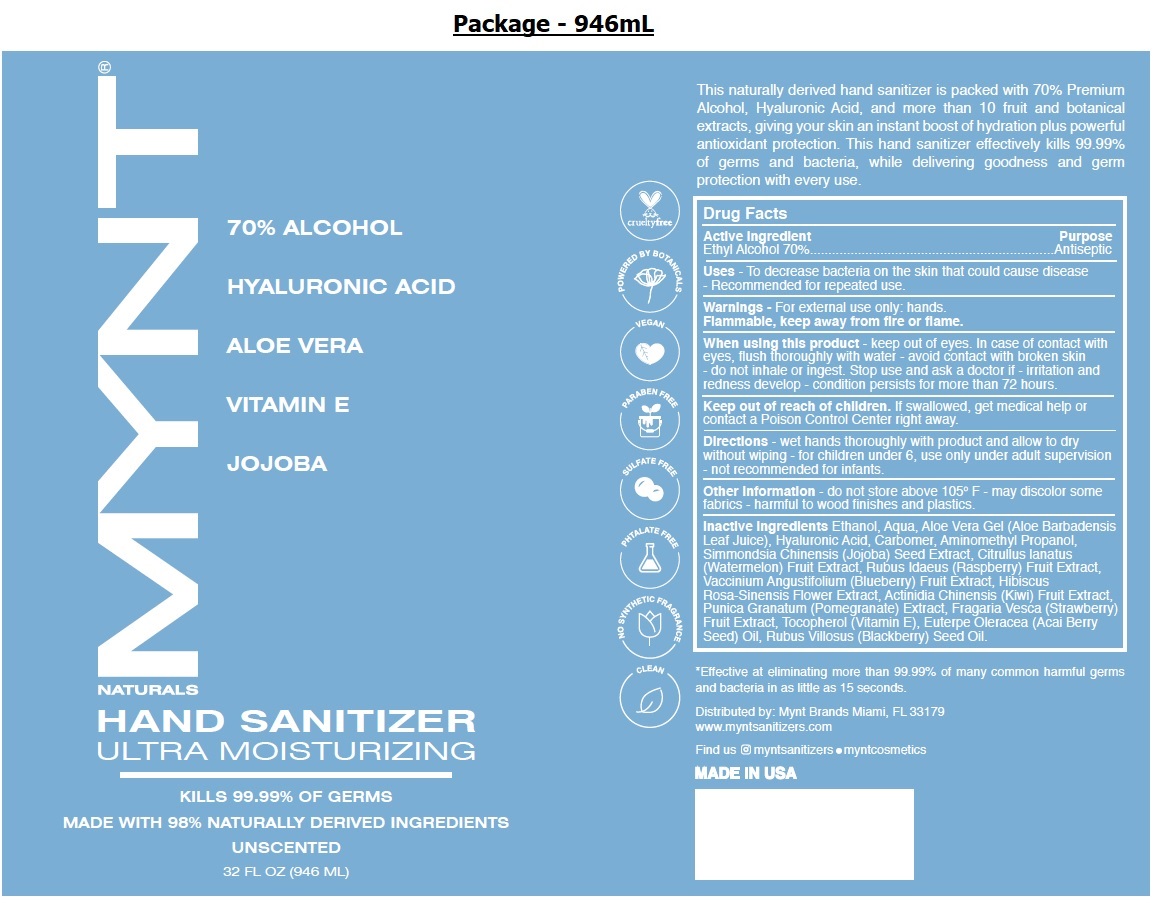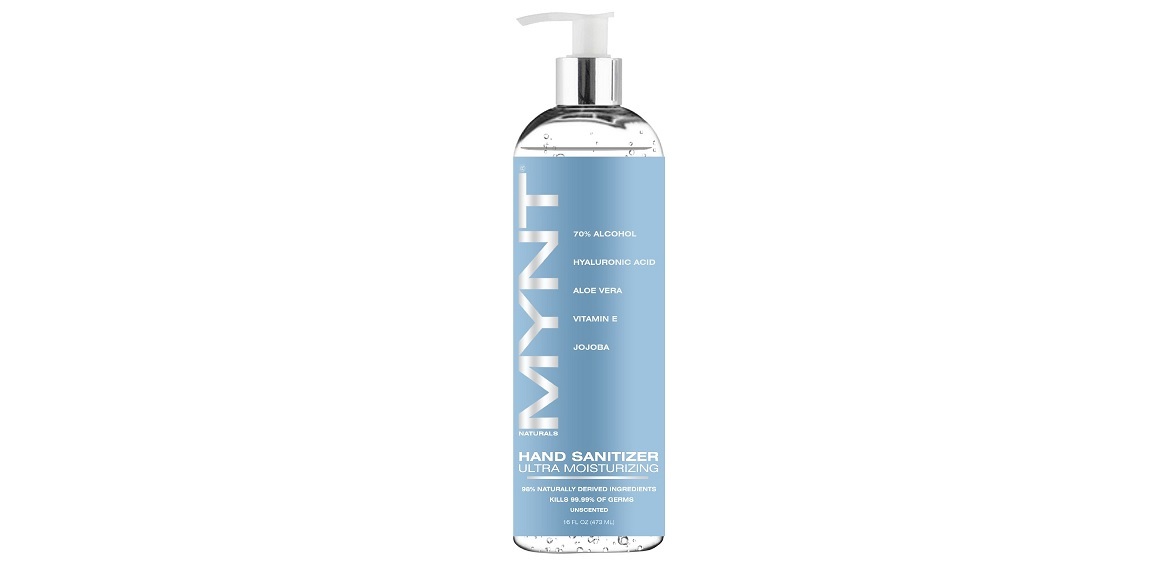 DRUG LABEL: MYNT NATURALS Hand Sanitizer Ultra Moisturizing
NDC: 79442-101 | Form: GEL
Manufacturer: Prive International Inc.
Category: otc | Type: HUMAN OTC DRUG LABEL
Date: 20200929

ACTIVE INGREDIENTS: ALCOHOL 70 mL/100 mL
INACTIVE INGREDIENTS: WATER; ALOE VERA LEAF; HYALURONIC ACID; CARBOMER HOMOPOLYMER, UNSPECIFIED TYPE; AMINOMETHYLPROPANOL; SIMMONDSIA CHINENSIS SEED; WATERMELON; RASPBERRY; LOWBUSH BLUEBERRY; HIBISCUS ROSA-SINENSIS FLOWER; KIWI FRUIT; PUNICA GRANATUM ROOT BARK; FRAGARIA VESCA FRUIT; TOCOPHEROL; ACAI OIL; RUBUS CORCHORIFOLIUS WHOLE

MYNT® NATURALS HAND SANITIZER ULTRA MOISTURIZING UNSCENTED

Active ingredient

Ethyl Alcohol 70%

Purpose

Antiseptic

INDICATIONS AND USAGE

Uses - To decrease bacteria on the skin that could cause disease - Recommended for repeated use.

Warnings - For external use only: hands.

Flammable, keep away from fire or flame.

When using this product - keep out of eyes. In case of contact with eyes, flush thoroughly with water - avoid contact with broken skin - do not inhale or ingest. Stop use and ask a doctor if - irritation and redness develop - condition persists for more than 72 hours.

Keep out of reach of children. If swallowed, get medical help or contact a Poison Control Center right away.

DOSAGE AND ADMINISTRATION

Directions - wet hands thoroughly with product and allow to dry without wiping - for children under 6, use only under adult supervision - not recommended for infants.

Other information - do not store above 105° F - may discolor some fabrics - harmful to wood finishes and plastics.

INACTIVE INGREDIENT

Inactive ingredients Ethanol, Aqua, Aloe Vera Gel (Aloe Barbadensis Leaf Juice), Hyaluronic Acid, Carbomer, Aminomethyl Propanol, Simmondsia Chinensis (Jojoba) Seed Extract, Citrullus lanatus (Watermelon) Fruit Extract, Rubus Idaeus (Raspberry) Fruit Extract, Vaccinium Angustifolium (Blueberry) Fruit Extract, Hibiscus Rosa-Sinensis Flower Extract, Actinidia Chinensis (Kiwi) Fruit Extract, Punica Granatum (Pomegranate) Extract, Fragaria Vesca (Strawberry) Fruit Extract, Tocopherol (Vitamin E), Euterpe Oleracea (Acai Berry Seed) Oil, Rubus Villosus (Blackberry) Seed Oil.

70% ALCOHOL

HYALURONIC ACID

ALOE VERA

VITAMIN E

JOJOBA

KILLS 99.99% OF GERMS

MADE WITH 98% NATURALLY DERIVED INGREDIENTS

UNSCENTED

cruelty free

POWERED BY BOTANICALS

VEGAN

PARABEN FREE

SULFATE FREE

PHTALATE FREE

NO SYNTHETIC FRAGRANCE

CLEAN

This naturally derived hand sanitizer is packed with 70% Premium Alcohol, Hyaluronic Acid, and more than 10 fruit and botanical extracts, giving your skin an instant boost of hydration plus powerful antioxidant protection. This hand sanitizer effectively kills 99.99% of germs and bacteria, while delivering goodness and germ protection with every use.

*Effective at eliminating more than 99.99% of many common harmful germs and bacteria in as little as 15 seconds.

Distributed by: Mynt Brands Miami, FL 33179

www.myntsanitizers.com

Find us myntsanitizers • myntcosmetics

MADE IN USA